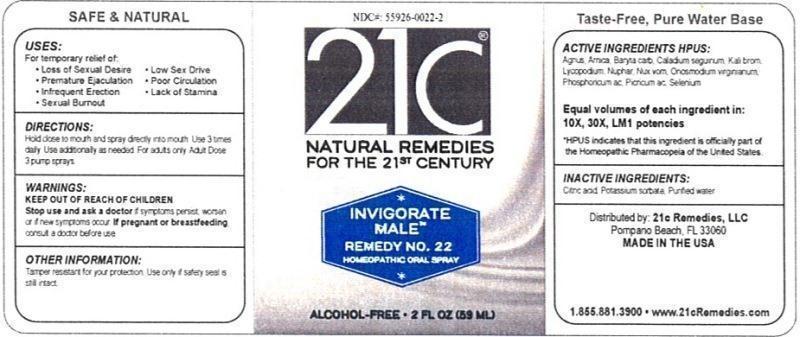 DRUG LABEL: Invigorate Male Remedy No. 22
NDC: 55926-0022 | Form: LIQUID
Manufacturer: Speer Laboratories, LLC
Category: homeopathic | Type: HUMAN OTC DRUG LABEL
Date: 20130801

ACTIVE INGREDIENTS: CHASTE TREE 10 [hp_X]/59 mL; ARNICA MONTANA 10 [hp_X]/59 mL; BARIUM CARBONATE 10 [hp_X]/59 mL; DIEFFENBACHIA SEGUINE 10 [hp_X]/59 mL; POTASSIUM BROMIDE 10 [hp_X]/59 mL; LYCOPODIUM CLAVATUM SPORE 10 [hp_X]/59 mL; NUPHAR LUTEUM ROOT 10 [hp_X]/59 mL; STRYCHNOS NUX-VOMICA SEED 10 [hp_X]/59 mL; ONOSMODIUM VIRGINIANUM WHOLE 10 [hp_X]/59 mL; PHOSPHORIC ACID 10 [hp_X]/59 mL; PICRIC ACID 10 [hp_X]/59 mL; SELENIUM 10 [hp_X]/59 mL
INACTIVE INGREDIENTS: CITRIC ACID MONOHYDRATE; POTASSIUM SORBATE; WATER

Invigorate Male Remedy No. 22

ACTIVE INGREDIENT

Active Ingredients HPUS: Agnus castus, Arnica montana, Baryta carbonica, Caladium seguinum, Kali bromatum, Lycopodium clavatum, Nuphar luteum, Nux vomica, Onosmodium virginianum, Phosphoricum acidum, Picricum acidum, Selenium metallicum.

Equal volumes of each ingredient in: 10X, 30X, LM1 potencies

HPUS indicates that this ingredient is officially part of the Homeopathic Pharmacopeia of the United States.

Inactive Ingredients: Citric acid, Potassium sorbate, Purified water.

INDICATIONS AND USAGE

Uses: For temporary relief of:

- loss of sexual desire
- premature ejaculation
- infrequent erection
- sexual burnout
- low sex drive
- poor circulation
- lack of stamina

Directions:

Hold close to mouth and spray directly into mouth. Use 3 times daily. Use additionally as needed. For adults only. Adult dose: 3 pump sprays.

Keep out of reach of children.

WARNINGS

Warnings: Stop use and ask a doctor if symptoms persist, worsen or if new symptoms occur. If pregnant or breastfeeding, consult a doctor before use.

OTHER SAFETY INFORMATION

Tamper resistant for your protection. Use only if safety seal is still intact.

PURPOSE

Uses: For temporary relief of: loss of sexual desire, premature ejaculation,infrequent erection, sexual burnout, low sex drive, poor circulation, lack of stamina